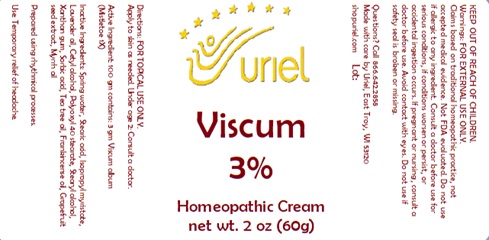 DRUG LABEL: Viscum 3
NDC: 48951-9049 | Form: CREAM
Manufacturer: Uriel Pharmacy Inc.
Category: homeopathic | Type: HUMAN OTC DRUG LABEL
Date: 20241216

ACTIVE INGREDIENTS: VISCUM ALBUM FRUITING TOP 1 [hp_X]/1 g
INACTIVE INGREDIENTS: TEA TREE OIL; SORBIC ACID; LAVENDER OIL; WATER; STEARIC ACID; ISOPROPYL MYRISTATE; CETYL ALCOHOL; POLYOXYL 40 STEARATE; STEARYL ALCOHOL; XANTHAN GUM; FRANKINCENSE OIL; MYRRH OIL; CITRUS PARADISI SEED

Viscum 3%

INDICATIONS AND USAGE

Directions: FOR TOPICAL USE ONLY.

DOSAGE AND ADMINISTRATION

Apply to skin as needed. Under age 2: Consult a doctor.

Active Ingredient: 100 gm contains: 3 gm Viscum album (Mistletoe) 1X

INACTIVE INGREDIENT

Inactive Ingredients: Spring water, Stearic acid, Isopropyl myristate, Lavender oil, Cetyl alcohol, Polyoxyl 40 stearate, Stearyl alcohol, Xanthan gum, Sorbic acid, Tea tree oil, Frankincense oil, Grapefruit seed extract, Myrrh oil

Prepared using rhythmical processes.

PURPOSE

Use: Temporary relief of headache.

KEEP OUT OF REACH OF CHILDREN.

Warnings: FOR EXTERNAL USE ONLY.
Claims based on traditional homeopathic practice, not accepted medical evidence. Not FDA evaluated. Do not use if allergic to any ingredient. Consult a doctor before use for serious conditions, if conditions worsen or persist, or accidental ingestion occurs. If pregnant or nursing, consult a doctor before use. Avoid contact with eyes. Do not use if safety seal is broken or missing.

QUESTIONS

Questions? Call 866.642.2858 Made with care by Uriel, East Troy, WI 53120 shopuriel.com Lot: